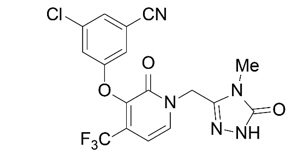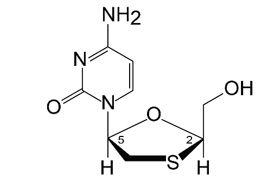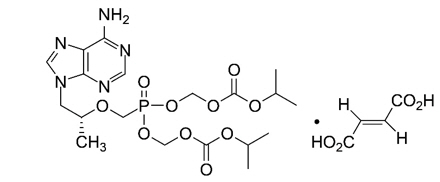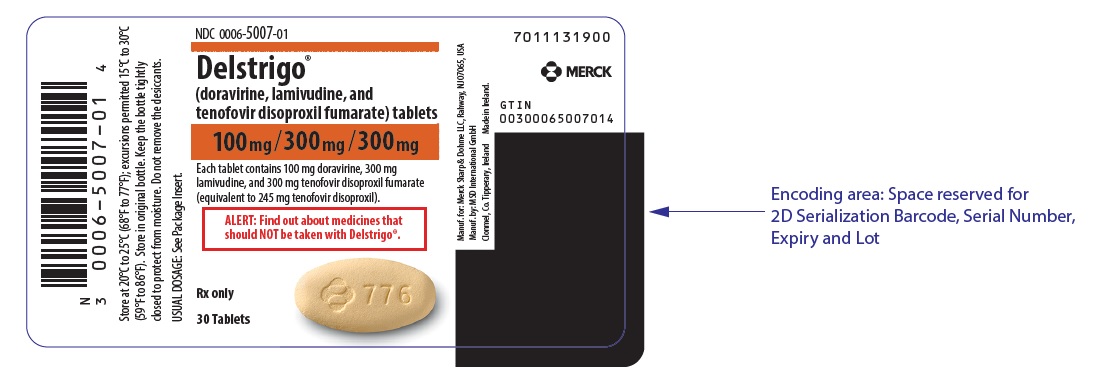 DRUG LABEL: DELSTRIGO
NDC: 0006-5007 | Form: TABLET, FILM COATED
Manufacturer: Merck Sharp & Dohme LLC
Category: prescription | Type: HUMAN PRESCRIPTION DRUG LABEL
Date: 20251029

ACTIVE INGREDIENTS: doravirine 100 mg/1 1; lamivudine 300 mg/1 1; tenofovir disoproxil fumarate 300 mg/1 1
INACTIVE INGREDIENTS: silicon dioxide; croscarmellose sodium; hypromellose acetate succinate 06081224 (3 MM2/S); magnesium stearate; microcrystalline cellulose; sodium stearyl fumarate; carnauba wax; hypromellose, unspecified; ferric oxide yellow; lactose monohydrate; titanium dioxide; triacetin

HIGHLIGHTS OF PRESCRIBING INFORMATION

These highlights do not include all the information needed to use DELSTRIGO safely and effectively. See full prescribing information for DELSTRIGO.
DELSTRIGO® (doravirine, lamivudine, and tenofovir disoproxil fumarate) tablets, for oral use
Initial U.S. Approval: 2018

RECENT MAJOR CHANGES

Warnings and Precautions (5.1) | 11/2024
Warnings and Precautions (5.5) | 06/2025

WARNING: POSTTREATMENT ACUTE EXACERBATION OF HEPATITIS B

See full prescribing information for complete boxed warning.

Severe acute exacerbations of hepatitis B (HBV) have been reported in people with concomitant HIV-1 and HBV who have discontinued lamivudine or tenofovir disoproxil fumarate (TDF), two of the components of DELSTRIGO. Closely monitor hepatic function in these patients. If appropriate, initiation of anti-hepatitis B therapy may be warranted. (5.2)

1 INDICATIONS AND USAGE

DELSTRIGO is a three-drug combination of doravirine (a non-nucleoside reverse transcriptase inhibitor [NNRTI]), lamivudine, and tenofovir disoproxil fumarate (both nucleoside analogue reverse transcriptase inhibitors) and is indicated as a complete regimen for the treatment of HIV-1 infection in adults and pediatric patients weighing at least 35 kg:

- with no antiretroviral treatment history, OR
- to replace the current antiretroviral regimen in those who are virologically-suppressed (HIV-1 RNA less than 50 copies per mL) on a stable antiretroviral regimen with no history of treatment failure and no known substitutions associated with resistance to the individual components of DELSTRIGO. (1)

2 DOSAGE AND ADMINISTRATION

- Testing: Prior to or when initiating DELSTRIGO, test for HBV infection. Prior to or when initiating DELSTRIGO, and during treatment with DELSTRIGO, on a clinically appropriate schedule, assess serum creatinine, estimated creatinine clearance, urine glucose and urine protein in all patients. In patients with chronic kidney disease, also assess serum phosphorus. (2.1)
- Recommended dosage: One tablet taken orally once daily with or without food in adults and pediatric patients weighing at least 35 kg. (2.2)
- Renal impairment: Not recommended in patients with estimated creatinine clearance below 50 mL per minute. (2.3)
- Dosage adjustment with rifabutin: Take one tablet of DELSTRIGO once daily, followed by one tablet of doravirine 100 mg (PIFELTRO) approximately 12 hours after the dose of DELSTRIGO. (2.4)

3 DOSAGE FORMS AND STRENGTHS

- Tablets: 100 mg of doravirine, 300 mg of lamivudine, and 300 mg of tenofovir disoproxil fumarate. (3)

4 CONTRAINDICATIONS

- DELSTRIGO is contraindicated when co-administered with drugs that are strong cytochrome P450 (CYP)3A enzyme inducers as significant decreases in doravirine plasma concentrations may occur, which may decrease the effectiveness of DELSTRIGO. (4)
- DELSTRIGO is contraindicated in patients with a previous hypersensitivity reaction to lamivudine.

5 WARNINGS AND PRECAUTIONS

- Severe skin reactions, including Stevens-Johnson syndrome (SJS)/toxic epidermal necrolysis (TEN), have been reported during the postmarketing experience with doravirine-containing regimens. Discontinue DELSTRIGO, and other medications known to be associated with severe skin reactions, immediately if a painful rash with mucosal involvement or a progressive severe rash develops, and closely monitor clinical status. (5.1)
- New onset or worsening renal impairment: Prior to or when initiating DELSTRIGO, and during treatment with DELSTRIGO, on a clinically appropriate schedule, assess serum creatinine, estimated creatinine clearance, urine glucose, and urine protein in all patients. Avoid administering DELSTRIGO with concurrent or recent use of nephrotoxic drugs. (5.3)
- Bone loss and mineralization defects: Consider monitoring BMD in patients with a history of pathologic fracture or other risk factors of osteoporosis or bone loss. (5.5)
- Monitor for Immune Reconstitution Syndrome. (5.6)

6 ADVERSE REACTIONS

Most common adverse reactions (incidence greater than or equal to 5%, all grades) are dizziness, nausea, and abnormal dreams. (6.1)

To report SUSPECTED ADVERSE REACTIONS, contact Merck Sharp & Dohme LLC at 1-877-888-4231 or FDA at 1-800-FDA-1088 or www.fda.gov/medwatch.

7 DRUG INTERACTIONS

- Because DELSTRIGO is a complete regimen, co-administration with other antiretroviral medications for treatment of HIV-1 infection is not recommended. (7.1)
- Consult the full prescribing information prior to and during treatment for important potential drug-drug interactions. (4, 5.4, 7)

8 USE IN SPECIFIC POPULATIONS

- Pediatrics: Not recommended for patients weighing less than 35 kg. (8.4)

FULL PRESCRIBING INFORMATION

WARNING: POSTTREATMENT ACUTE EXACERBATION OF HEPATITIS B

Severe acute exacerbations of hepatitis B (HBV) have been reported in people with concomitant HIV-1 and HBV who have discontinued lamivudine or tenofovir disoproxil fumarate (TDF), which are components of DELSTRIGO. Hepatic function should be monitored closely with both clinical and laboratory follow-up for at least several months in patients who are coinfected with HIV-1 and HBV and discontinue DELSTRIGO. If appropriate, initiation of anti-hepatitis B therapy may be warranted [see Warnings and Precautions (5.2)].

1 INDICATIONS AND USAGE

DELSTRIGO® is indicated as a complete regimen for the treatment of HIV-1 infection in adults and pediatric patients weighing at least 35 kg:

- with no prior antiretroviral treatment history, OR
- to replace the current antiretroviral regimen in those who are virologically-suppressed (HIV-1 RNA less than 50 copies per mL) on a stable antiretroviral regimen with no history of treatment failure and no known substitutions associated with resistance to the individual components of DELSTRIGO [see Clinical Studies (14)].

2 DOSAGE AND ADMINISTRATION

2.1 Testing When Initiating and During Treatment with DELSTRIGO

Prior to or when initiating DELSTRIGO, test patients for HBV infection [see Warnings and Precautions (5.2)].

Prior to or when initiating DELSTRIGO, and during treatment with DELSTRIGO, on a clinically appropriate schedule, assess serum creatinine, estimated creatinine clearance, urine glucose, and urine protein in all patients. In patients with chronic kidney disease, also assess serum phosphorus [see Warnings and Precautions (5.3)].

2.2 Recommended Dosage

DELSTRIGO is a fixed-dose combination product containing 100 mg of doravirine (DOR), 300 mg of lamivudine (3TC), and 300 mg of TDF. The recommended dosage of DELSTRIGO in adults and pediatric patients weighing at least 35 kg is one tablet taken orally once daily with or without food [see Clinical Pharmacology (12.3)].

2.3 Renal Impairment

Because DELSTRIGO is a fixed-dose combination tablet and the dosage of lamivudine and TDF cannot be adjusted, DELSTRIGO is not recommended in patients with estimated creatinine clearance less than 50 mL/min [see Warnings and Precautions (5.3) and Use in Specific Populations (8.6)].

2.4 Dosage Adjustment with Rifabutin

If DELSTRIGO is co-administered with rifabutin, take one tablet of DELSTRIGO once daily, followed by one tablet of doravirine 100 mg (PIFELTRO) approximately 12 hours after the dose of DELSTRIGO for the duration of rifabutin co-administration [see Drug Interactions (7.2) and Clinical Pharmacology (12.3)].

3 DOSAGE FORMS AND STRENGTHS

DELSTRIGO film-coated tablets are yellow, oval-shaped tablets, debossed with the corporate logo and 776 on one side and plain on the other side. Each tablet contains 100 mg doravirine, 300 mg lamivudine, and 300 mg tenofovir disoproxil fumarate (equivalent to 245 mg of tenofovir disoproxil).

4 CONTRAINDICATIONS

- DELSTRIGO is contraindicated when co-administered with drugs that are strong cytochrome P450 (CYP)3A enzyme inducers as significant decreases in doravirine plasma concentrations may occur, which may decrease the effectiveness of DELSTRIGO [see Warnings and Precautions (5.4), Drug Interactions (7.2), and Clinical Pharmacology (12.3)]. These drugs include, but are not limited to, the following:
  - the anticonvulsants carbamazepine, oxcarbazepine, phenobarbital, phenytoin
  - the androgen receptor inhibitor enzalutamide
  - the antimycobacterials rifampin, rifapentine
  - the cytotoxic agent mitotane
  - St. John's wort (Hypericum perforatum)
- DELSTRIGO is contraindicated in patients with a previous hypersensitivity reaction to lamivudine.

5 WARNINGS AND PRECAUTIONS

5.1 Severe Skin Reactions

Severe skin reactions, including Stevens-Johnson syndrome (SJS)/toxic epidermal necrolysis (TEN), have been reported during the postmarketing experience with doravirine-containing regimens [see Adverse Reactions (6.2)]. Discontinue DELSTRIGO, and other medications known to be associated with severe skin reactions, immediately if a painful rash with mucosal involvement or a progressive severe rash develops. Clinical status should be closely monitored, and appropriate therapy should be initiated.

5.2 Severe Acute Exacerbation of Hepatitis B in People with Concomitant HIV-1 and HBV

All patients with HIV-1 should be tested for the presence of HBV before initiating antiretroviral therapy.

Severe acute exacerbations of hepatitis B (e.g., liver decompensated and liver failure) have been reported in people with concomitant HIV-1 and HBV who have discontinued products containing lamivudine and/or TDF, and may occur with discontinuation of DELSTRIGO. Patients who are coinfected with HIV-1 and HBV who discontinue DELSTRIGO should be closely monitored with both clinical and laboratory follow-up for at least several months after stopping treatment with DELSTRIGO. If appropriate, initiation of anti-hepatitis B therapy may be warranted, especially in patients with advanced liver disease or cirrhosis, since post-treatment exacerbation of hepatitis may lead to hepatic decompensation and liver failure.

5.3 New Onset or Worsening Renal Impairment

Renal impairment, including cases of acute renal failure and Fanconi syndrome (renal tubular injury with severe hypophosphatemia), has been reported with the use of TDF, a component of DELSTRIGO.

DELSTRIGO should be avoided with concurrent or recent use of a nephrotoxic agent (e.g., high-dose or multiple nonsteroidal anti-inflammatory drugs [NSAIDs]) [see Drug Interactions (7.1)]. Cases of acute renal failure after initiation of high-dose or multiple NSAIDs have been reported in patients living with HIV with risk factors for renal dysfunction who appeared stable on TDF. Some patients required hospitalization and renal replacement therapy. Alternatives to NSAIDs should be considered, if needed, in patients at risk for renal dysfunction.

Persistent or worsening bone pain, pain in extremities, fractures, and/or muscular pain or weakness may be manifestations of proximal renal tubulopathy and should prompt an evaluation of renal function in at-risk patients.

Prior to or when initiating DELSTRIGO, and during treatment with DELSTRIGO, on a clinically appropriate schedule, assess serum creatinine, estimated creatinine clearance, urine glucose and urine protein in all patients. In patients with chronic kidney disease, also assess serum phosphorus. Discontinue DELSTRIGO in patients who develop clinically significant decreases in renal function or evidence of Fanconi syndrome.

The lamivudine and TDF components of DELSTRIGO are primarily excreted by the kidney. Discontinue DELSTRIGO if estimated creatinine clearance declines below 50 mL/min as dose interval adjustment required for lamivudine and TDF cannot be achieved with the fixed-dose combination tablet [see Use in Specific Populations (8.6)].

5.4 Risk of Adverse Reactions or Loss of Virologic Response Due to Drug Interactions

The concomitant use of DELSTRIGO and certain other drugs may result in known or potentially significant drug interactions, some of which may lead to [see Dosage and Administration (2.4), Contraindications (4), and Drug Interactions (7.2)]:

- Loss of therapeutic effect of DELSTRIGO and possible development of resistance.
- Possible clinically significant adverse reactions from greater exposures of a component of DELSTRIGO.

See Table 6 for steps to prevent or manage these possible and known significant drug interactions, including dosing recommendations. Consider the potential for drug interactions prior to and during DELSTRIGO therapy, review concomitant medications during DELSTRIGO therapy, and monitor for adverse reactions.

5.5 Bone Loss and Mineralization Defects

Bone Mineral Density

In clinical trials in adults living with HIV, TDF (a component of DELSTRIGO) was associated with slightly greater decreases in bone mineral density (BMD) and increases in biochemical markers of bone metabolism, suggesting increased bone turnover relative to comparators. Serum parathyroid hormone levels and 1,25 Vitamin D levels were also higher in participants receiving TDF.

Clinical trials evaluating TDF in pediatric participants were conducted. Under normal circumstances, BMD increases rapidly in pediatric patients. In participants 2 years to less than 18 years of age living with HIV, bone effects were similar to those observed in adult participants and suggest increased bone turnover. Total body BMD gain was less in the TDF-treated pediatric participants living with HIV as compared to the control groups. Similar trends were observed in chronic HBV-infected pediatric participants 2 years to less than 18 years of age. In all pediatric trials, normal skeletal growth (height) was not affected for the duration of the clinical trials.

The effects of TDF-associated changes in BMD and biochemical markers on long-term bone health and future fracture risk in adults and pediatric participants 2 years and older are unknown. The long-term effect of lower spine and total body BMD on skeletal growth in pediatric patients, and in particular, the effects of long-duration exposure in younger children are unknown.

Assessment of BMD should be considered for adult and pediatric patients living with HIV who have a history of pathologic bone fracture or other risk factors for osteoporosis or bone loss. Although the effect of supplementation with calcium and vitamin D was not studied, such supplementation may be beneficial in all patients. If bone abnormalities are suspected, then appropriate consultation should be obtained.

Mineralization Defects

Cases of osteomalacia associated with proximal renal tubulopathy, manifested as bone pain or pain in extremities and which may contribute to fractures, have been reported in association with the use of TDF [see Adverse Reactions (6.2)]. Arthralgias and muscle pain or weakness have also been reported in cases of proximal renal tubulopathy. Hypophosphatemia and osteomalacia secondary to proximal renal tubulopathy should be considered in patients at risk of renal dysfunction who present with persistent or worsening bone or muscle symptoms while receiving products containing TDF [see Warnings and Precautions (5.3)].

5.6 Immune Reconstitution Syndrome

Immune reconstitution syndrome has been reported in patients treated with combination antiretroviral therapy. During the initial phase of combination antiretroviral treatment, patients whose immune system responds may develop an inflammatory response to indolent or residual opportunistic infections (such as Mycobacterium avium infection, cytomegalovirus, Pneumocystis jirovecii pneumonia (PCP), or tuberculosis), which may necessitate further evaluation and treatment.

Autoimmune disorders (such as Graves' disease, polymyositis, Guillain-Barré syndrome, and autoimmune hepatitis) have also been reported to occur in the setting of immune reconstitution; however, the time to onset is more variable and can occur many months after initiation of treatment.

6 ADVERSE REACTIONS

The following adverse reactions are discussed in other sections of the labeling:

- Severe Acute Exacerbation of Hepatitis B in people with concomitant HIV-1 and HBV [see Warnings and Precautions (5.2)]
- New Onset or Worsening Renal Impairment [see Warnings and Precautions (5.3)]
- Bone Loss and Mineralization Defects [see Warnings and Precautions (5.5)]
- Immune Reconstitution Syndrome [see Warnings and Precautions (5.6)]

6.1 Clinical Trials Experience

Because clinical trials are conducted under widely varying conditions, adverse reaction rates observed in the clinical trials of a drug cannot be directly compared to rates in the clinical trials of another drug and may not reflect the rates observed in practice.

Adverse Reactions in Adults with No Antiretroviral Treatment History

The safety assessment of DELSTRIGO is based on Week 96 data from two Phase 3, randomized, international, multicenter, double-blind, active-controlled trials. A total of 747 participants received doravirine either as the single entity in combination with other antiretroviral drugs as background regimens (n=383) or as the fixed-dose DELSTRIGO (n=364), and a total of 747 participants were randomized to control arms.

In DRIVE-AHEAD (Protocol 021), 728 adult participants received either DELSTRIGO (n=364) or EFV/FTC/TDF once daily (n=364). By Week 96, 3% in the DELSTRIGO group and 7% in the EFV/FTC/TDF group had adverse events leading to discontinuation of study medication.

Adverse reactions reported in greater than or equal to 5% of participants in any treatment group in DRIVE-AHEAD are presented in Table 1.

Table 1: Adverse Reactions [Frequencies of adverse reactions are based on all adverse events attributed to trial drugs by the investigator.] (All Grades) Reported in ≥5% [No adverse reactions of Grade 2 or higher (moderate or severe) occurred in ≥2% of participants treated with DELSTRIGO.] of Participants in Any Treatment Group in Adults with No Antiretroviral Treatment History in DRIVE-AHEAD (Week 96)
 | DELSTRIGO Once Daily N=364 | EFV/FTC/TDF Once Daily N=364
Dizziness | 7% | 32%
Nausea | 5% | 7%
Abnormal Dreams | 5% | 10%
Headache | 4% | 5%
Insomnia | 4% | 5%
Diarrhea | 4% | 6%
Somnolence | 3% | 7%
Rash [Rash: includes rash, rash erythematous, rash generalized, rash macular, rash maculo-papular, rash papular, rash pruritic.] | 2% | 12%

The majority (66%) of adverse reactions associated with DELSTRIGO occurred at severity Grade 1 (mild).

Neuropsychiatric Adverse Events

For DRIVE-AHEAD, the analysis of participants with neuropsychiatric adverse events by Week 48 is presented in Table 2. The proportion of participants who reported one or more neuropsychiatric adverse events was 24% and 57% in the DELSTRIGO and EFV/FTC/TDF groups, respectively.

A statistically significantly lower proportion of DELSTRIGO-treated participants compared to EFV/FTC/TDF-treated participants reported neuropsychiatric adverse events by Week 48 in the three pre-specified categories of dizziness, sleep disorders and disturbances, and altered sensorium.

Table 2: DRIVE-AHEAD - Analysis of Participants with Neuropsychiatric Adverse Events [All causality and all grade events were included in the analysis.] (Week 48)
 | DELSTRIGO Once Daily N=364 | EFV/FTC/TDF Once Daily N=364 | Treatment Difference (DELSTRIGO - EFV/FTC/TDF) Estimate (95% CI) [The 95% CIs were calculated using Miettinen and Nurminen's method. Categories pre-specified for statistical testing were dizziness (p <0.001), sleep disorders and disturbances (p <0.001), and altered sensorium (p=0.033).]
Sleep disorders and disturbances [Predefined using MedDRA preferred terms including: abnormal dreams, hyposomnia, initial insomnia, insomnia, nightmare, sleep disorder, somnambulism.] | 12% | 26% | -13.5 (-19.1, -7.9)
Dizziness | 9% | 37% | -28.3 (-34.0, -22.5)
Altered sensorium [Predefined using MedDRA preferred terms including: altered state of consciousness, lethargy, somnolence, syncope.] | 4% | 8% | -3.8 (-7.6, -0.3)

Neuropsychiatric adverse events in the pre-defined category of depression and suicide/self-injury were reported in 4% and 7% of participants, in the DELSTRIGO and EFV/FTC/TDF groups, respectively.

In DRIVE-AHEAD through 48 weeks of treatment, the majority of participants who reported neuropsychiatric adverse events reported events that were mild to moderate in severity (97% [83/86] and 96% [198/207], in the DELSTRIGO and EFV/FTC/TDF groups, respectively) and the majority of participants reported these events in the first 4 weeks of treatment (72% [62/86] in the DELSTRIGO group and 86% [177/207] in the EFV/FTC/TDF group).

Neuropsychiatric adverse events led to treatment discontinuation in 1% (2/364) and 1% (5/364) of participants in the DELSTRIGO and EFV/FTC/TDF groups, respectively. The proportion of participants who reported neuropsychiatric adverse events through Week 4 was 17% (62/364) in the DELSTRIGO group and 49% (177/364) in the EFV/FTC/TDF group. At Week 48, the prevalence of neuropsychiatric adverse events was 12% (44/364) in the DELSTRIGO group and 22% (81/364) in the EFV/FTC/TDF group. At Week 96, the prevalence of neuropsychiatric adverse events was 13% (47/364) in the DELSTRIGO group and 23% (82/364) in the EFV/FTC/TDF group.

Laboratory Abnormalities

The percentages of participants with selected laboratory abnormalities (that represent a worsening from baseline) who were treated with DELSTRIGO or EFV/FTC/TDF in DRIVE-AHEAD are presented in Table 3.

Table 3: Selected Laboratory Abnormalities Reported in Adult Participants with No Antiretroviral Treatment History in DRIVE-AHEAD (Week 96)
Laboratory Parameter Preferred Term (Unit)/Limit | DELSTRIGO Once Daily N=364 | EFV/FTC/TDF Once Daily N=364
Blood Chemistry
Total bilirubin (mg/dL)
1.1 - <1.6 × ULN | 5% | 0%
1.6 - <2.6 × ULN | 2% | 0%
≥2.6 × ULN | 1% | <1%
Creatinine (mg/dL)
>1.3 - 1.8 × ULN or Increase of >0.3 mg/dL above baseline | 3% | 2%
>1.8 × ULN or Increase of ≥1.5 × above baseline | 3% | 2%
Aspartate aminotransferase (IU/L)
2.5 - <5.0 × ULN | 3% | 3%
≥5.0 × ULN | 1% | 4%
Alanine aminotransferase (IU/L)
2.5 - <5.0 × ULN | 4% | 4%
≥5.0 × ULN | 1% | 3%
Alkaline phosphatase (IU/L)
2.5 - <5.0 × ULN | <1% | 1%
≥5.0 × ULN | 0% | <1%
Lipase
1.5 - <3.0 × ULN | 6% | 4%
≥3.0 × ULN | 2% | 3%
Creatine kinase (IU/L)
6.0 - <10.0 × ULN | 3% | 3%
≥10.0 × ULN | 4% | 6%
Cholesterol, fasted (mg/dL)
≥300 mg/dL | 1% | <1%
LDL cholesterol, fasted (mg/dL)
≥190 mg/dL | <1% | 2%
Triglycerides, fasted (mg/dL)
>500 mg/dL | 1% | 3%
Each participant is only counted once per parameter at the highest toxicity grade. Only participants with a baseline value and at least one on-treatment value for a given laboratory parameter are included.
ULN = Upper limit of normal range.

Change in Lipids from Baseline

For DRIVE-AHEAD, changes from baseline at Week 48 in LDL-cholesterol, non-HDL-cholesterol, total cholesterol, triglycerides, and HDL-cholesterol are shown in Table 4. Changes from baseline at Week 96 were similar to findings at Week 48.

The LDL and non-HDL comparisons were pre-specified and are summarized in Table 4. The differences were statistically significant, showing superiority of DELSTRIGO for both parameters. The clinical benefit of these findings has not been demonstrated.

Table 4: Mean Change from Baseline in Fasting Lipids in Adult Participants with No Antiretroviral Treatment History in DRIVE-AHEAD (Week 48)
Laboratory Parameter Preferred Term | DELSTRIGO Once Daily N=320 |  | EFV/FTC/TDF Once Daily N=307 |  | Difference Estimates (DELSTRIGO - EFV/FTC/TDF)
 | Baseline | Change | Baseline | Change | Difference (95% CI)
LDL-Cholesterol (mg/dL) [p-value for the pre-specified hypothesis testing for treatment difference was <0.0001.] | 91.7 | -2.1 | 91.3 | 8.3 | -10.2 (-13.8, -6.7)
Non-HDL Cholesterol (mg/dL) | 114.7 | -4.1 | 115.3 | 12.7 | -16.9 (-20.8, -13.0)
Total Cholesterol (mg/dL) [Not pre-specified for hypothesis testing.] | 156.8 | -2.2 | 156.8 | 21.1 | -
Triglycerides (mg/dL) | 118.7 | -12.0 | 122.6 | 21.6 | -
HDL-Cholesterol (mg/dL) | 42.1 | 1.8 | 41.6 | 8.4 | -
Participants on lipid-lowering agents at baseline were excluded from these analyses (DELSTRIGO n=15 and EFV/FTC/TDF n=10).
Participants initiating a lipid-lowering agent post-baseline had their last fasted on-treatment value (prior to starting the agent) carried forward (DELSTRIGO n=3 and EFV/FTC/TDF n=8).

Adverse Reactions in Virologically-Suppressed Adults

The safety of DELSTRIGO in virologically-suppressed adults was based on Week 48 data from 670 participants in the DRIVE-SHIFT trial (Protocol 024), a randomized, international, multicenter, open-label trial in which virologically-suppressed participants were switched from a baseline regimen consisting of two nucleoside reverse transcriptase inhibitors (NRTIs) in combination with a protease inhibitor (PI) plus either ritonavir or cobicistat, or elvitegravir plus cobicistat, or an NNRTI to DELSTRIGO. Overall, the safety profile in virologically-suppressed adult participants was similar to that in participants with no antiretroviral treatment history.

Laboratory Abnormalities

Serum ALT and AST Elevations: In the DRIVE-SHIFT trial, 22% and 16% of participants in the immediate switch group experienced ALT and AST elevations of greater than 1.25 × ULN, respectively, through 48 weeks on DELSTRIGO. For these ALT and AST elevations, no apparent time patterns with regard to time to onset relative to switch were observed. One percent of participants had ALT or AST elevations greater than 5 × ULN through 48 weeks on DELSTRIGO. The ALT and AST elevations were generally asymptomatic, and not associated with bilirubin elevations. In comparison, 4% and 4% of participants in the delayed switch group experienced ALT and AST elevations of greater than 1.25 × ULN through 24 weeks on their baseline regimen.

Change in Lipids from Baseline

Changes from baseline at Week 24 in LDL-cholesterol, non-HDL-cholesterol, total cholesterol, triglycerides, and HDL-cholesterol in participants on a PI plus ritonavir-based regimen at baseline are shown in Table 5. The LDL and non-HDL comparisons were pre-specified, and the differences were statistically significant, showing superiority for an immediate switch to DELSTRIGO for both parameters. The clinical benefit of these findings has not been demonstrated.

Table 5: Mean Change from Baseline in Fasting Lipids in Adult Virologically-Suppressed Participants on a PI plus Ritonavir-based Regimen at Baseline in DRIVE-SHIFT (Week 24)
Laboratory Parameter Preferred Term | DELSTRIGO (Week 0-24) Once Daily N=244 |  | PI+ritonavir (Week 0-24) Once Daily N=124 |  | Difference Estimates
 | Baseline | Change | Baseline | Change | Difference (95% CI)
LDL-Cholesterol (mg/dL) [p-value for the pre-specified hypothesis testing for treatment difference was <0.0001.] | 108.7 | -16.3 | 110.5 | -2.6 | -14.5 (-18.9, -10.1)
Non-HDL Cholesterol (mg/dL) | 138.6 | -24.8 | 138.8 | -2.1 | -22.8 (-27.9, -17.7)
Total Cholesterol (mg/dL) [Not pre-specified for hypothesis testing.] | 188.5 | -26.1 | 187.4 | -0.2 | -
Triglycerides (mg/dL) | 153.1 | -44.4 | 151.4 | -0.4 | -
HDL-Cholesterol (mg/dL) | 50.0 | -1.3 | 48.5 | 1.9 | -
Participants on lipid-lowering agents at baseline were excluded from these analyses (DELSTRIGO n=26 and PI+ritonavir n=13).
Participants initiating a lipid-lowering agent post-baseline had their last fasted on-treatment value (prior to starting the agent) carried forward (DELSTRIGO n=4 and PI+ritonavir n=2).

Adverse Reactions in Pediatric Participants

The safety of DELSTRIGO was evaluated in 45 virologically-suppressed or treatment-naïve pediatric participants 12 to less than 18 years of age living with HIV, through Week 24 in an open-label trial (IMPAACT 2014 (Protocol 027)) [see Clinical Studies (14.3)]. The safety profile in pediatric participants was similar to that in adults. There were no serious or Grade 3 or 4 adverse reactions. No participants discontinued due to an adverse event.

6.2 Postmarketing Experience

The following adverse reactions have been identified during postmarketing experience in patients receiving doravirine-, lamivudine- or TDF-containing regimens. Because postmarketing reactions are reported voluntarily from a population of uncertain size, it is not always possible to reliably estimate their frequency or establish a causal relationship to drug exposure.

Doravirine:

Skin and Subcutaneous Tissue Disorders: Stevens-Johnson syndrome (SJS)/toxic epidermal necrolysis (TEN)

Hepatobiliary Disorders: hepatitis

Investigations: hepatic enzyme increased

Lamivudine:

Body as a Whole: redistribution/accumulation of body fat

Endocrine and Metabolic: hyperglycemia

General: Weakness

Hemic and Lymphatic: anemia (including pure red cell aplasia and severe anemias progressing on therapy)

Hepatic and Pancreatic: lactic acidosis and hepatic steatosis, posttreatment exacerbations of hepatitis B

Hypersensitivity: anaphylaxis, urticaria

Musculoskeletal: muscle weakness, CPK elevation, rhabdomyolysis

Skin: alopecia, pruritus

TDF:

Immune System Disorders: allergic reaction, including angioedema

Metabolism and Nutrition Disorders: lactic acidosis, hypokalemia, hypophosphatemia

Respiratory, Thoracic, and Mediastinal Disorders: dyspnea

Gastrointestinal Disorders: pancreatitis, increased amylase, abdominal pain

Hepatobiliary Disorders: hepatic steatosis, hepatitis, increased liver enzymes (most commonly AST, ALT gamma GT)

Skin and Subcutaneous Tissue Disorders: rash

Musculoskeletal and Connective Tissue Disorders: rhabdomyolysis, osteomalacia (manifested as bone pain and which may contribute to fractures), muscular weakness, myopathy

Renal and Urinary Disorders: acute renal failure, renal failure, acute tubular necrosis, Fanconi syndrome, proximal renal tubulopathy, interstitial nephritis (including acute cases), nephrogenic diabetes insipidus, renal insufficiency, increased creatinine, proteinuria, polyuria

General Disorders and Administration Site Conditions: asthenia

The following adverse reactions, listed under the body system headings above, may occur as a consequence of proximal renal tubulopathy: rhabdomyolysis, osteomalacia, hypokalemia, muscular weakness, myopathy, hypophosphatemia.

7 DRUG INTERACTIONS

7.1 Concomitant Use with Other Antiretroviral Medications

Because DELSTRIGO is a complete regimen for the treatment of HIV-1 infection, co-administration with other antiretroviral medications for treatment of HIV-1 infection is not recommended. Information regarding potential drug-drug interactions with other antiretroviral medications is not provided.

7.2 Effect of Other Drugs on DELSTRIGO

Co-administration of DELSTRIGO with a CYP3A inducer decreases doravirine plasma concentrations, which may reduce DELSTRIGO efficacy [see Contraindications (4), Warnings and Precautions (5.4), and Clinical Pharmacology (12.3)].

Co-administration of DELSTRIGO and drugs that are inhibitors of CYP3A may result in increased plasma concentrations of doravirine.

Table 6 shows the significant drug interactions with the components of DELSTRIGO. The drug interactions described are based on studies conducted with either DELSTRIGO or the components of DELSTRIGO as individual agents.

Table 6: Drug Interactions with DELSTRIGO [This table is not all-inclusive]
Concomitant Drug Class: Drug Name | Effect on Concentration | Clinical Comment
Androgen Receptors
enzalutamide | ↓ doravirine | Co-administration is contraindicated with enzalutamide. At least a 4-week cessation period is recommended prior to initiation of DELSTRIGO.
Anticonvulsants
carbamazepine oxcarbazepine phenobarbital phenytoin | ↓ doravirine | Co-administration is contraindicated with these anticonvulsants. At least a 4-week cessation period is recommended prior to initiation of DELSTRIGO.
Antimycobacterials
rifampin [The interaction between doravirine and the concomitant drug was evaluated in a clinical study.] rifapentine | ↓ doravirine | Co-administration is contraindicated with rifampin or rifapentine. At least a 4-week cessation period is recommended prior to initiation of DELSTRIGO.
rifabutin | ↓ doravirine | If DELSTRIGO is co-administered with rifabutin, one tablet of doravirine (PIFELTRO) should be taken approximately 12 hours after the dose of DELSTRIGO [see Dosage and Administration (2.4)].
Cytotoxic Agents
mitotane | ↓ doravirine | Co-administration is contraindicated with mitotane. At least a 4-week cessation period is recommended prior to initiation of DELSTRIGO.
Hepatitis C Antiviral Agents
ledipasvir/sofosbuvir sofosbuvir/velpatasvir | ↑ tenofovir | Monitor for adverse reactions associated with TDF.
Herbal Products
St. John's wort | ↓ doravirine | Co-administration is contraindicated with St. John's wort. At least a 4-week cessation period is recommended prior to initiation of DELSTRIGO.
Other Agents
sorbitol | ↓ lamivudine | Co-administration of single doses of lamivudine and sorbitol resulted in a sorbitol dose-dependent reduction in lamivudine exposures. When possible, avoid use of sorbitol-containing medicines with lamivudine-containing medicines.
↑ = increase, ↓ = decrease
All other drug-drug interactions shown are anticipated based on the known metabolic and elimination pathways.

Co-administration of DELSTRIGO with drugs that reduce renal function or compete for active tubular secretion may increase serum concentrations of lamivudine, tenofovir, and/or other renally eliminated drugs. Some examples of drugs that are eliminated by active tubular secretion include, but are not limited to, acyclovir, cidofovir, ganciclovir, valacyclovir, valganciclovir, aminoglycosides (e.g., gentamicin), and high-dose or multiple NSAIDs [see Warnings and Precautions (5.3) and Clinical Pharmacology (12.3)].

No clinically significant changes in concentration were observed for doravirine when co-administered with the following agents: TDF, lamivudine, elbasvir and grazoprevir, ledipasvir and sofosbuvir, ritonavir, ketoconazole, aluminum hydroxide/magnesium hydroxide/simethicone containing antacid, pantoprazole, or methadone [see Clinical Pharmacology (12.3)].

No clinically significant changes in concentration were observed for tenofovir when co-administered with tacrolimus or entecavir [see Clinical Pharmacology (12.3)].

7.3 Effect of DELSTRIGO on Other Drugs

No clinically significant changes in concentration were observed for the following agents when co-administered with doravirine: lamivudine, TDF, elbasvir and grazoprevir, ledipasvir and sofosbuvir, atorvastatin, an oral contraceptive containing ethinyl estradiol and levonorgestrel, metformin, methadone, or midazolam.

No clinically significant drug interactions have been observed between TDF and the following medications: entecavir, methadone, oral contraceptives, sofosbuvir, or tacrolimus in studies conducted in healthy participants.

Lamivudine is not significantly metabolized by CYP enzymes nor does it inhibit or induce this enzyme system; therefore, it is unlikely that clinically significant drug interactions will occur through these pathways [see Clinical Pharmacology (12.3)].

8 USE IN SPECIFIC POPULATIONS

8.1 Pregnancy

Pregnancy Exposure Registry

There is a pregnancy exposure registry that monitors pregnancy outcomes in individuals exposed to DELSTRIGO during pregnancy. Healthcare providers are encouraged to register patients by calling the Antiretroviral Pregnancy Registry (APR) at 1-800-258-4263.

Risk Summary

There is insufficient prospective pregnancy data from the APR to adequately assess the risk of birth defects and miscarriage. Doravirine use in individuals during pregnancy has not been evaluated; however, lamivudine and TDF use during pregnancy has been evaluated in a limited number of individuals reported to the APR. Available data from the APR show no difference in the overall risk of major birth defects for lamivudine and TDF compared with the background rate for major birth defects of 2.7% in the U.S. reference population of the Metropolitan Atlanta Congenital Defects Program (MACDP) (see Data). The rate of miscarriage is not reported in the APR. The estimated background rate of miscarriage in the clinically recognized pregnancies in the U.S. general population is 15-20%. Methodological limitations of the APR include the use of MACDP as the external comparator group. The MACDP population is not disease-specific, evaluates individuals and infants from the limited geographic area, and does not include outcomes for births that occurred at less than 20 weeks gestation.

In animal reproduction studies, oral administration of lamivudine to pregnant rabbits during organogenesis resulted in embryolethality at systemic exposure (AUC) similar to the recommended clinical dose; however, no adverse development effects were observed with oral administration of lamivudine to pregnant rats during organogenesis at plasma concentrations (Cmax) 35 times the recommended clinical dose.

No adverse developmental effects were observed when doravirine and TDF were administered separately at doses/exposures ≥8 (doravirine) and ≥14 (TDF) times those of the recommended human dose (RHD) of DELSTRIGO (see Data).

Data

Human Data

Lamivudine: The APR has received a total of over 13,000 prospective reports with follow-up data of possible exposure to lamivudine-containing regimens; over 5,900 reports in the first trimester; over 5,600 reports in the second trimester; and over 1,800 reports in the third trimester. Birth defects occurred in 170 of 5,472 (3.1%, 95% CI: 2.7% to 3.6%) live births for lamivudine-containing regimens (first trimester exposure); and 218 of 7,513 (2.9%, 95% CI: 2.5% to 3.3%) live births for lamivudine-containing regimens (second/third trimester exposure). Among pregnant mothers in the U.S. reference population, the background rate of birth defects is 2.7%. There was no association between lamivudine and overall birth defects observed in the APR.

TDF: The APR has received a total of over 7,000 prospective reports with follow-up data of possible exposure to tenofovir disoproxil-containing regimens; over 5,100 reports in the first trimester; over 1,300 reports in the second trimester; and over 600 reports in the third trimester. Birth defects occurred in 113 of 4,576 (2.5%, 95% CI: 2.0% to 3.0%) live births for TDF-containing regimens (first trimester exposure); and 51 of 1,965 (2.6%, 95% CI: 1.9% to 3.4%) live births for TDF-containing regimens (second/third trimester exposure). Among pregnant mothers in the U.S. reference population, the background rate of birth defects is 2.7%. There was no association between tenofovir and overall birth defects observed in the APR.

Animal Data

Doravirine: Doravirine was administered orally to pregnant rabbits (up to 300 mg/kg/day on gestation days (GD) 7 to 20) and rats (up to 450 mg/kg/day on GD 6 to 20 and separately from GD 6 to lactation/postpartum day 20). No significant toxicological effects on embryo-fetal (rats and rabbits) or pre/post-natal (rats) development were observed at exposures (AUC) approximately 9 times (rats) and 8 times (rabbits) the exposure in humans at the RHD. Doravirine was transferred to the fetus through the placenta in embryo-fetal studies, with fetal plasma concentrations of up to 40% (rabbits) and 52% (rats) that of maternal concentrations observed on GD 20.

Lamivudine: Lamivudine was administered orally to pregnant rats (at 90, 600, and 4,000 mg per kg per day) and rabbits (at 90, 300, and 1,000 mg per kg per day and at 15, 40, and 90 mg per kg per day) during organogenesis (on GD 7 through 16 [rat] and 8 through 20 [rabbit]). No evidence of fetal malformations due to lamivudine was observed in rats and rabbits at doses producing plasma concentrations (Cmax) approximately 35 times higher than human exposure at the recommended daily dose. Evidence of early embryolethality was seen in the rabbit at system exposures (AUC) similar to those observed in humans, but there was no indication of this effect in the rat at plasma concentrations (Cmax) 35 times higher than human exposure at the recommended daily dose. Studies in pregnant rats showed that lamivudine is transferred to the fetus through the placenta. In the fertility/pre- and postnatal development study in rats, lamivudine was administered orally at doses of 180, 900, and 4,000 mg per kg per day (from prior to mating through postnatal Day 20). In the study, development of the offspring, including fertility and reproductive performance, was not affected by maternal administration of lamivudine.

TDF: Reproduction studies have been performed in rats and rabbits at doses up to 14 and 19 times the human dose based on body surface area comparisons and revealed no evidence of harm to the fetus.

8.2 Lactation

Risk Summary

Based on limited published data, both lamivudine and tenofovir are present in human milk. It is unknown whether doravirine is present in human milk, but doravirine is present in the milk of lactating rats (see Data). It is not known whether DELSTRIGO or the components of DELSTRIGO affects human milk production, or has effects on the breastfed infant. Potential risks of breastfeeding include: (1) HIV-1 transmission (in HIV-1-negative infants), (2) developing viral resistance (in HIV-1-positive infants), and (3) serious adverse reactions in a breastfed infant similar to those seen in adults.

Data

Doravirine: Doravirine was excreted into the milk of lactating rats following oral administration (450 mg/kg/day) from GD 6 to lactation day 14, with milk concentrations approximately 1.5 times that of maternal plasma concentrations observed 2 hours post dose on lactation day 14.

8.4 Pediatric Use

The safety and efficacy of DELSTRIGO for the treatment of HIV-1 infection have been established in pediatric patients weighing at least 35 kg [see Indications and Usage (1) and Dosage and Administration (2.2)].

Use of DELSTRIGO in this group is supported by evidence from adequate and well-controlled trials in adults with additional pharmacokinetic, safety, and efficacy data from an open-label trial in virologically-suppressed or treatment-naïve pediatric participants 12 to less than 18 years of age. The safety and efficacy of DELSTRIGO in these pediatric participants were similar to that in adults, and there was no clinically significant difference in exposure for the components of DELSTRIGO. [see Adverse Reactions (6.1), Clinical Pharmacology (12.3), and Clinical Studies (14.3)].

Safety and efficacy of DELSTRIGO in pediatric patients weighing less than 35 kg have not been established.

8.5 Geriatric Use

Clinical trials of doravirine, lamivudine, or TDF did not include sufficient numbers of participants aged 65 years and over to determine whether they respond differently from younger participants. In general, caution should be exercised in the administration of DELSTRIGO in elderly patients reflecting the greater frequency of decreased hepatic, renal, or cardiac function, and of concomitant disease or other drug therapy [see Clinical Pharmacology (12.3)].

8.6 Renal Impairment

Because DELSTRIGO is a fixed-dose combination tablet and the dosage of lamivudine and TDF, both components of DELSTRIGO, cannot be altered, DELSTRIGO is not recommended in patients with estimated creatinine clearance less than 50 mL/min [see Warnings and Precautions (5.3) and Clinical Pharmacology (12.3)].

8.7 Hepatic Impairment

No dosage adjustment of DELSTRIGO is required in patients with mild (Child-Pugh Class A) or moderate (Child-Pugh Class B) hepatic impairment. DELSTRIGO has not been studied in patients with severe hepatic impairment (Child-Pugh Class C) [see Clinical Pharmacology (12.3)].

10 OVERDOSAGE

No data are available on overdose of DELSTRIGO in patients and there is no known specific treatment for overdose with DELSTRIGO. If overdose occurs, the patient should be monitored and standard supportive treatment applied as required.

Doravirine: There is no known specific treatment for overdose with doravirine.

Lamivudine: Because a negligible amount of lamivudine was removed via (4-hour) hemodialysis, continuous ambulatory peritoneal dialysis, and automated peritoneal dialysis, it is not known if continuous hemodialysis would provide clinical benefit in a lamivudine overdose event.

TDF: TDF is efficiently removed by hemodialysis with an extraction coefficient of approximately 54%. Following a single 300 mg dose of TDF, a 4-hour hemodialysis session removed approximately 10% of the administered tenofovir dose.

11 DESCRIPTION

DELSTRIGO is a fixed-dose combination, film-coated tablet, containing doravirine, lamivudine, and TDF for oral administration.

Doravirine is an HIV-1 non-nucleoside reverse transcriptase inhibitor (NNRTI).

Lamivudine is the (-)enantiomer of a dideoxy analogue of cytidine and is an HIV-1 nucleoside analogue reverse transcriptase inhibitor.

TDF (a prodrug of tenofovir) is a fumaric acid salt of the bis-isopropoxycarbonyloxymethyl ester derivative of tenofovir. In vivo TDF is converted to tenofovir, an acyclic nucleoside phosphonate (nucleotide) analog of adenosine 5'-monophosphate. Tenofovir is an HIV-1 reverse transcriptase inhibitor.

Each tablet contains 100 mg of doravirine, 300 mg of lamivudine, and 300 mg of TDF (equivalent to 245 mg of tenofovir disoproxil) as active ingredients. The tablets include the following inactive ingredients: colloidal silicon dioxide, croscarmellose sodium, hypromellose acetate succinate, magnesium stearate, microcrystalline cellulose, and sodium stearyl fumarate. The tablets are film coated with a coating material containing the following inactive ingredients: hypromellose, iron oxide yellow, lactose monohydrate, titanium dioxide, and triacetin. The coated tablets are polished with carnauba wax.

Doravirine:

The chemical name for doravirine is 3-chloro-5-[[1-[(4,5-dihydro-4-methyl-5-oxo-1H-1,2,4-triazol-3-yl)methyl]-1,2-dihydro-2-oxo-4-(trifluoromethyl)-3-pyridinyl]oxy]benzonitrile.

It has a molecular formula of C17H11ClF3N5O3 and a molecular weight of 425.75.

It has the following structural formula:

Doravirine is practically insoluble in water.

Lamivudine:

The chemical name for lamivudine is (-)-1-[(2R,5S)-2-(hydroxymethyl)-1,3-oxathiolan-5-yl]-cytosine.

It has a molecular formula of C8H11N3O3S and a molecular weight of 229.26.

It has the following structural formula:

Lamivudine is soluble in water.

TDF:

The chemical name for TDF is 9-[(R)-2-[[bis[[(isopropoxycarbonyl)oxy]methoxy] phosphinyl]- methoxy]propyl]adenine fumarate (1:1).

It has a molecular formula of C19H30N5O10 P∙C4H4O4 and a molecular weight of 635.52.

It has the following structural formula:

TDF is slightly soluble in water.

12 CLINICAL PHARMACOLOGY

12.1 Mechanism of Action

DELSTRIGO is a fixed-dose combination of the antiretroviral drugs doravirine, lamivudine, and TDF [see Microbiology (12.4)].

12.2 Pharmacodynamics

In a Phase 2 trial evaluating doravirine over a dose range of 0.25 to 2 times the recommended dose of doravirine in DELSTRIGO (in combination with FTC/TDF) in participants living with HIV with no antiretroviral treatment history, no exposure-response relationship for efficacy was identified for doravirine.

Cardiac Electrophysiology

At a doravirine dose of 1200 mg, which provides approximately 4 times the peak concentration observed following the recommended dose of doravirine in DELSTRIGO does not prolong the QT interval to any clinically relevant extent.

12.3 Pharmacokinetics

Single-dose administration of one DELSTRIGO tablet to healthy participants provided comparable exposures of doravirine, lamivudine, and tenofovir to administration of doravirine tablets (100 mg) plus lamivudine tablets (300 mg) plus TDF tablets (300 mg). Doravirine pharmacokinetics are similar in healthy participants and participants living with HIV. Pharmacokinetic properties of the components of DELSTRIGO are provided in Table 7.

Table 7: Pharmacokinetic Properties of the Components of DELSTRIGO
Parameter | Doravirine | Lamivudine | Tenofovir
General
Steady State Exposure [Presented as geometric mean (%CV: geometric coefficient of variation) or mean ± SD.]
AUC0-24 (mcg∙h/mL) | 16.1 (29) [Doravirine 100 mg once daily to participants living with HIV.] | 8.87 ± 1.83 [Lamivudine 300 mg once daily for 7 days to 60 healthy participants.] | 2.29 ± 0.69 [Single 300 mg dose of TDF to participants living with HIV in the fasted state.]
Cmax (mcg/mL) | 0.962 (19) | 2.04 ± 0.54 | 0.30 ± 0.09
C24 (mcg/mL) | 0.396 (63) | NA | NA
Absorption
Absolute Bioavailability | 64% | 86% | 25%
Tmax (h) | 2 | NA | 1
Effect of Food [Geometric mean ratio [high-fat meal/fasting] and (90% confidence interval) for PK parameters. High fat meal is approximately 1000 kcal, 50% fat. The effect of food is not clinically relevant.]
AUC Ratio | 1.10 (1.01, 1.20) | 0.93 (0.84, 1.03) | 1.27 (1.17, 1.37)
Cmax Ratio | 0.95 (0.80, 1.12) | 0.81 (0.65, 1.01) | 0.88 (0.74, 1.04)
C24 Ratio | 1.26 (1.13, 1.41) | NA | NA
Distribution
Vdss [Based on IV dose.] | 60.5 L | 1.3 L/kg | 1.3 L/kg
Plasma Protein Binding | 76% | < 36% | <0.7%
Elimination
t1/2 (h) | 15 | 5-7 | 17
CL/F (mL/ min) | 106 (35.2) | 398.5 ± 69.1 | 1,043.7 ± 115.4
CLrenal (mL/ min) | 9.3 (18.6) | 199.7 ± 56.9 | 243.5 ± 33.3
Metabolism
Primary Pathway(s) | CYP3A | Minor | No CYP Metabolism
Excretion
Major route of elimination | Metabolism | Glomerular filtration and active tubular secretion | Glomerular filtration and active tubular secretion
Urine (unchanged) | 6% | 71% | 70-80%
Biliary/Fecal (unchanged) | Minor | NA | NA
Abbreviations: NA=not available; AUC=area under the time concentration curve; Cmax=maximum concentration; C24=concentration at 24 hours; Tmax=time to Cmax; Vdss=apparent volume of distribution at steady state; t1/2=elimination half-life; CL/F=apparent clearance; CLrenal = renal clearance

Specific Populations

In adults, no clinically significant differences in the pharmacokinetics of certain DELSTRIGO components were observed based on age ≥65 years (for doravirine), sex (for doravirine, lamivudine, tenofovir), and race/ethnicity (for doravirine, lamivudine). The effects of age (≥65 years) on the pharmacokinetics of lamivudine and tenofovir, and the effect of race on the pharmacokinetics of tenofovir are unknown.

Patients with Renal Impairment

Doravirine: No clinically significant difference in the pharmacokinetics of doravirine were observed in participants with mild to severe renal impairment (creatinine clearance (CLcr) >15 mL/min, estimated by Cockcroft-Gault). Doravirine has not been studied in patients with end-stage renal disease or in patients undergoing dialysis.

Lamivudine: The AUC∞, Cmax, and half-life of lamivudine increased and CL/F decreased to a clinically significant extent with diminishing renal function (CLcr 111 to < 10 mL/min).

TDF: A clinically significant increase in the Cmax and AUC of tenofovir was observed in participants with CLcr < 50 mL/min or with end stage renal disease requiring dialysis [see Warnings and Precautions (5.3) and Use in Specific Populations (8.6)].

Patients with Hepatic Impairment

Doravirine: No clinically significant difference in the pharmacokinetics of doravirine was observed in participants with moderate hepatic impairment (Child-Pugh score B) compared to participants without hepatic impairment. Doravirine has not been studied in participants with severe hepatic impairment (Child-Pugh score C).

Lamivudine: No clinically significant differences in lamivudine pharmacokinetics were observed with diminishing hepatic function. Safety and efficacy of lamivudine have not been established in the presence of decompensated liver disease.

TDF: No clinically significant differences in tenofovir pharmacokinetics were observed between participants with any degree of hepatic impairment and unimpaired participants.

Pediatric Patients

Mean doravirine exposures were similar in 54 pediatric participants aged 12 to less than 18 years and weighing at least 35 kg who received doravirine or DELSTRIGO in IMPAACT 2014 (Protocol 027) relative to adults following administration of doravirine or DELSTRIGO. Exposures of lamivudine and tenofovir in pediatric participants following the administration of DELSTRIGO were similar to those in adults following administration of lamivudine and tenofovir (Table 8). For pediatric participants weighing ≥ 35 kg and < 45 kg who receive doravirine 100 mg or DELSTRIGO, the population pharmacokinetic model-predicted mean C24 of doravirine was comparable to that achieved in adults, whereas mean AUC0-24 and Cmax of doravirine were 25% and 36% higher than adult values, respectively. However, the predicted AUC0-24 and Cmax increases are not considered clinically significant.

Table 8: Steady State Pharmacokinetics for Doravirine, Lamivudine, and Tenofovir Following Administration of Doravirine or DELSTRIGO in Pediatric Participants Living with HIV Aged 12 to Less than 18 Years and Weighing at Least 35 kg
Parameter [Presented as geometric mean (%CV: geometric coefficient of variation)] | Doravirine [From population PK analysis (n=53 weighing ≥45 kg, n=1 weighing ≥35 kg to <45 kg)] | Lamivudine [From intensive PK analysis (n=10)] | Tenofovir
AUC0-24 (mcg•h/mL) | 16.4 (24) | 11.3 (28) | 2.55 (14)
Cmax (mcg/mL) | 1.03 (16) | 2.1 (24) | 0.293 (37)
C24 (mcg/mL) | 0.379 (42) | NA | NA
Abbreviations: NA=not applicable; AUC=area under the time concentration curve; Cmax=maximum concentration; C24=concentration at 24 hours

Drug Interaction Studies

DELSTRIGO is a complete regimen for the treatment of HIV-1 infection; therefore, DELSTRIGO is not recommended to be administered with other HIV-1 antiretroviral medications. Information regarding potential drug-drug interactions with other antiretroviral medications is not provided.

The drug interaction trials described were conducted with doravirine, lamivudine and/or TDF, as single entities; no drug interaction trials have been conducted using the combination of doravirine, lamivudine, and TDF. No clinically relevant drug interactions were observed between doravirine, lamivudine, and TDF.

Doravirine: Doravirine is primarily metabolized by CYP3A, and drugs that induce or inhibit CYP3A may affect the clearance of doravirine. Co-administration of doravirine and drugs that induce CYP3A may result in decreased plasma concentrations of doravirine. Co-administration of doravirine and drugs that inhibit CYP3A may result in increased plasma concentrations of doravirine.

Doravirine is not likely to have a clinically relevant effect on the exposure of medicinal products metabolized by CYP enzymes. Doravirine did not inhibit major drug metabolizing enzymes in vitro, including CYPs 1A2, 2B6, 2C8, 2C9, 2C19, 2D6, 3A4, and UGT1A1 and is not likely to be an inducer of CYP1A2, 2B6, or 3A4. Based on in vitro assays, doravirine is not likely to be an inhibitor of OATP1B1, OATP1B3, P-glycoprotein, BSEP, OAT1, OAT3, OCT2, MATE1, and MATE2K. Drug interaction studies were performed with doravirine and other drugs likely to be co-administered or commonly used as probes for pharmacokinetic interactions. The effects of co-administration with other drugs on the exposure (Cmax, AUC, and C24) of doravirine are summarized in Table 9. A single doravirine 100 mg dose was administered in these studies unless otherwise noted.

Table 9: Drug Interactions: Changes in Pharmacokinetic Parameter Values of Doravirine in the Presence of Co-administered Drug
Co-administered Drug | Regimen of Co-administered Drug | N | Geometric Mean Ratio (90% CI) of Doravirine Pharmacokinetics with/without Co-administered Drug (No Effect=1.00)
Co-administered Drug | Regimen of Co-administered Drug |  | AUC [AUC0-∞ for single-dose, AUC0-24 for once daily.] | Cmax | C24
Azole Antifungal Agents
ketoconazole [Changes in doravirine pharmacokinetic values are not clinically relevant.] | 400 mg QD | 10 | 3.06 (2.85, 3.29) | 1.25 (1.05, 1.49) | 2.75 (2.54, 2.98)
Antimycobacterials
rifampin | 600 mg QD | 10 | 0.12 (0.10, 0.15) | 0.43 (0.35, 0.52) | 0.03 (0.02, 0.04)
rifabutin | 300 mg QD | 12 | 0.50 (0.45, 0.55) | 0.99 (0.85, 1.15) | 0.32 (0.28, 0.35)
rifabutin | 300 mg QD [Doravirine 100 mg BID resulted in similar pharmacokinetic values when compared to 100 mg QD without rifabutin.] | 15 | 1.03 (0.94, 1.14) | 0.97 (0.87, 1.08) | 0.98 (0.88, 1.10)
HIV Antiviral Agents
ritonavir, [A single doravirine 50 mg dose (0.5 times the recommended approved dose) was administered.] | 100 mg BID | 8 | 3.54 (3.04, 4.11) | 1.31 (1.17, 1.46) | 2.91 (2.33, 3.62)
efavirenz | 600 mg QD [The first day following the cessation of efavirenz therapy and initiation of doravirine 100 mg QD.] | 17 | 0.38 (0.33, 0.45) | 0.65 (0.58, 0.73) | 0.15 (0.10, 0.23)
efavirenz | 600 mg QD [14 days following the cessation of efavirenz therapy and initiation of doravirine 100 mg QD.] | 17 | 0.68 (0.58, 0.80) | 0.86 (0.77, 0.97) | 0.50 (0.39, 0.64)
CI = confidence interval; QD = once daily; BID = twice daily

Based on drug interaction studies conducted with doravirine, no clinically significant drug interactions have been observed following the co-administration of doravirine and the following drugs: dolutegravir, TDF, lamivudine, elbasvir and grazoprevir, ledipasvir and sofosbuvir, ketoconazole, ritonavir, aluminum hydroxide/magnesium hydroxide/simethicone containing antacid, pantoprazole, atorvastatin, an oral contraceptive containing ethinyl estradiol and levonorgestrel, metformin, methadone, and midazolam.

Lamivudine:

Trimethoprim/Sulfamethoxazole: Co-administration of TMP/SMX with lamivudine resulted in an increase of 43% ±23% (mean ±SD) in lamivudine AUC∞, a decrease of 29% ±13% in lamivudine oral clearance, and a decrease of 30% ±36% in lamivudine renal clearance. The pharmacokinetic properties of TMP and SMX were not altered by co-administration with lamivudine.

Sorbitol (Excipient): Co-administration of lamivudine with a single dose of 3.2 grams, 10.2 grams, or 13.4 grams of sorbitol resulted in dose-dependent decreases of 14%, 32%, and 36% in the AUC∞; and 28%, 52%, and 55% in the Cmax of lamivudine, respectively.

TDF:

No clinically significant changes in exposure were observed for tenofovir when co-administered with tacrolimus or entecavir.

No clinically significant changes in exposure were observed for the following drugs when co-administered with tenofovir: tacrolimus, entecavir, methadone, or ethinyl estradiol/norgestimate.

12.4 Microbiology

Mechanism of Action

Doravirine: Doravirine is a pyridinone non-nucleoside reverse transcriptase inhibitor of HIV-1 and inhibits HIV-1 replication by non-competitive inhibition of HIV-1 reverse transcriptase (RT). The inhibitory concentration at 50% (IC50) of doravirine for RNA-dependent DNA polymerization of recombinant wild-type HIV-1 RT in a biochemical assay was 12.2±2.0 nM (n=3). Doravirine does not inhibit the human cellular DNA polymerases α, β, and mitochondrial DNA polymerase γ.

Lamivudine: Lamivudine is a synthetic nucleoside analogue. Intracellularly, lamivudine is phosphorylated to its active 5'-triphosphate metabolite, lamivudine triphosphate (3TC-TP). The principal mode of action of 3TC-TP is inhibition of RT via DNA chain termination after incorporation of the nucleotide analogue. Lamivudine triphosphate (3TC-TP) is a weak inhibitor of mammalian DNA polymerases α, β, and mitochondrial DNA polymerase γ.

TDF: TDF is an acyclic nucleoside phosphonate diester analog of adenosine monophosphate. TDF requires initial diester hydrolysis for conversion to tenofovir and subsequent phosphorylations by cellular enzymes to form tenofovir diphosphate. Tenofovir diphosphate inhibits the activity of HIV-1 RT by competing with the natural substrate deoxyadenosine 5'-triphosphate and, after incorporation into DNA, by DNA chain termination. Tenofovir diphosphate is a weak inhibitor of mammalian DNA polymerases α, β, and mitochondrial DNA polymerase γ.

Antiviral Activity in Cell Culture

Doravirine: Doravirine exhibited an EC50 value of 12.0±4.4 nM against wild-type laboratory strains of HIV-1 when tested in the presence of 100% normal human serum (NHS) using MT4-GFP reporter cells and a median EC50 value for HIV-1 subtype B primary isolates (n=118) of 4.1 nM (range: 1.0 nM-16.0 nM). Doravirine demonstrated antiviral activity against a broad panel of primary HIV-1 isolates (A, A1, AE, AG, B, BF, C, D, G, H) with EC50 values ranging from 1.2 nM to 10.0 nM. The antiviral activity of doravirine was not antagonistic when combined with lamivudine and TDF.

Lamivudine: The antiviral activity of lamivudine against HIV-1 was assessed in a number of cell lines including monocytes and peripheral blood mononuclear cells (PBMCs) using standard susceptibility assays. EC50 values were in the range of 3 to 15,000 nM (1,000 nM = 230 ng per mL). The median EC50 values of lamivudine were 60 nM (range: 20 to 70 nM), 35 nM (range: 30 to 40 nM), 30 nM (range: 20 to 90 nM), 20 nM (range: 3 to 40 nM), 30 nM (range: 1 to 60 nM), 30 nM (range: 20 to 70 nM), 30 nM (range: 3 to 70 nM), and 30 nM (range: 20 to 90 nM) against HIV-1 clades A-G and group O viruses (n = 3 except n = 2 for clade B) respectively. Ribavirin (50,000 nM) used in the treatment of chronic HCV infection decreased the anti-HIV-1 activity of lamivudine by 3.5-fold in MT-4 cells.

TDF: The antiviral activity of tenofovir against laboratory and clinical isolates of HIV-1 was assessed in T lymphoblastoid cell lines, primary monocyte/macrophage cells and peripheral blood lymphocytes. The EC50 values for tenofovir were in the range of 40-8,500 nM. Tenofovir displayed antiviral activity in cell culture against HIV-1 clades A, B, C, D, E, F, G, and O (EC50 values ranged from 500-2,200 nM).

Resistance

In Cell Culture

Doravirine: Doravirine-resistant strains were selected in cell culture starting from wild-type HIV-1 of different origins and subtypes, as well as NNRTI-resistant HIV-1. Observed emergent amino acid substitutions in RT included: V106A, V106I, V106M, V108I, H221Y, F227C, F227I, F227L, F227V, M230I, L234I, P236L, and Y318F. The V106A, V106M, V108I, H221Y, F227C, M230I, P236L, and Y318F substitutions conferred 3.4-fold to 70-fold reductions in susceptibility to doravirine. Y318F in combination with V106A, V106M, V108I, or F227C conferred greater decreases in susceptibility to doravirine than Y318F alone, which conferred a 10-fold reduction in susceptibility to doravirine.

Lamivudine: Lamivudine-resistant variants of HIV-1 have been selected in cell culture and in participants treated with lamivudine. Genotypic analysis showed that substitutions M184I or V cause resistance to lamivudine.

TDF: HIV-1 isolates selected by tenofovir in cell culture expressed a K65R substitution in HIV-1 RT and showed a 2–4 -fold reduction in susceptibility to tenofovir. In addition, a K70E substitution in HIV-1 RT has been selected by tenofovir and results in low-level reduced susceptibility to abacavir, emtricitabine, lamivudine, and tenofovir.

In Clinical Trials

Clinical Trial Results in Adults with No Antiretroviral Treatment History

Doravirine: In the doravirine treatment arm of the DRIVE-AHEAD trial (n=364) through 96 weeks, 10 participants showed the emergence of doravirine resistance-associated substitutions among 24 (42%) participants in the resistance analysis subset (participants with HIV-1 RNA greater than 400 copies per mL at virologic failure or early study discontinuation and having post-baseline resistance samples). Emergent doravirine resistance-associated substitutions in RT included one or more of the following: V90V/G, A98G, V106A, V106I, V106M/T, V108I, E138G, Y188L, H221Y, P225H, P225L, P225P/S, F227C, F227C/R, Y318Y/F, and Y318Y/S. Six of the 10 participants with emergent doravirine resistance-associated substitutions showed doravirine phenotypic resistance and all of them had a greater than 100-fold reduction in doravirine susceptibility (range >103 to >211). The other 4 virologic failures who had only amino acid mixtures of NNRTI resistance substitutions showed doravirine phenotypic fold-changes of less than 2-fold.

In the EFV/FTC/TDF treatment arm of the DRIVE-AHEAD trial (n=364) through Week 96, 15 participants showed the emergence of efavirenz resistance-associated substitutions among 25 (60%) participants in the resistance analysis subset.

Lamivudine and TDF: In a pooled analysis of antiretroviral-naïve participants who received doravirine, lamivudine, and TDF, genotyping was performed on plasma HIV-1 isolates from all participants with HIV-1 RNA greater than 400 copies per mL at confirmed virologic failure or at time of early study drug discontinuation. Genotypic resistance developed in 8 evaluable participants who received DOR/3TC/TDF through Week 96. The resistance–associated substitutions that emerged were RT M41L (n=1), A62A/V (n=1), K65R (n=2), T69T/A (n=1), V75V/I (n=1), and M184V (n=5). In comparison, genotypic resistance to emtricitabine or tenofovir developed in 5 evaluable participants who received EFV/FTC/TDF in DRIVE-AHEAD; emergent resistance-associated substitutions were RT K65R (n=1), D67G/K70E (n=1), L74V/V75M/V118I (n=1), M184I or V (n=5), and K219K/E (n=1).

Clinical Trial Results in Virologically-Suppressed Adults

In the DRIVE-SHIFT clinical trial [see Clinical Studies (14.2)], there were 6 participants in the immediate switch group (n=447) and 2 participants in the delayed switch group (n=209) who met the protocol-defined virologic failure criteria (confirmed HIV-1 RNA ≥ 50 copies/mL). Two of the 6 virologic failure participants in the immediate switch group had available resistance data and neither developed detectable genotypic or phenotypic resistance to doravirine, lamivudine, or tenofovir during treatment with DELSTRIGO. One of the two virologic failure participants in the delayed switch group who had available resistance data developed the RT M184M/I substitution and phenotypic resistance to emtricitabine and lamivudine during treatment with their baseline regimen.

Cross-Resistance

No significant cross-resistance has been demonstrated between doravirine-resistant HIV-1 variants and lamivudine/emtricitabine or tenofovir or between lamivudine or tenofovir-resistant variants and doravirine.

Doravirine: Cross-resistance has been observed among NNRTIs. Treatment-emergent doravirine resistance-associated substitutions can confer cross resistance to efavirenz, etravirine, nevirapine, and rilpivirine. Of the 6 virologic failure participants who developed doravirine phenotypic resistance, all had phenotypic resistance to efavirenz and nevirapine, 4 had phenotypic resistance to rilpivirine, and 4 had resistance to etravirine in the Monogram PhenoSense assay. Of the 11 virologic failure participants phenotypically resistant to efavirenz, 2 (18%) had decreased susceptibility to doravirine (18- and 36-fold).

The treatment-emergent doravirine resistance-associated substitution Y318F did not confer reduced susceptibility to efavirenz, etravirine, or rilpivirine.

A panel of 96 diverse clinical isolates containing NNRTI resistance-associated substitutions was evaluated for susceptibility to doravirine. Clinical isolates containing the Y188L substitution alone or in combination with K103N or V106I, V106A in combination with G190A and F227L, or E138K in combination with Y181C and M230L showed greater than 100-fold reduced susceptibility to doravirine.

Lamivudine: Cross-resistance has been observed among NRTIs. The M184I/V lamivudine resistance-associated substitution confers resistance to abacavir, didanosine and emtricitabine. Lamivudine also has reduced susceptibility against the K65R substitution.

TDF: Cross-resistance has been observed among NRTIs. The K65R substitution in HIV-1 RT selected by tenofovir is also selected in some patients living with HIV treated with abacavir or didanosine. HIV-1 isolates with the K65R substitution also showed reduced susceptibility to emtricitabine and lamivudine. Therefore, cross-resistance among these NRTIs may occur in patients whose virus harbors the K65R substitution. The K70E substitution selected clinically by TDF results in reduced susceptibility to abacavir, didanosine, emtricitabine, lamivudine, and tenofovir. HIV-1 isolates from patients (n=20) whose HIV-1 expressed a mean of 3 zidovudine resistance-associated substitutions (M41L, D67N, K70R, L210W, T215Y/F, or K219Q/E/N) showed a 3.1-fold decrease in the susceptibility to tenofovir. Participants whose virus expressed an RT L74V substitution without zidovudine resistance-associated substitutions (n=8) had reduced response to TDF. Limited data are available for patients whose virus expressed a Y115F substitution (n=3), Q151M substitution (n=2), or T69 insertion (n=4) in HIV-1 RT, all of whom had a reduced response in clinical trials.

13 NONCLINICAL TOXICOLOGY

13.1 Carcinogenesis, Mutagenesis, Impairment of Fertility

Carcinogenesis

Doravirine: Doravirine was not carcinogenic in long-term oral carcinogenicity studies in mice and rats at exposures up to 6 and 7 times, respectively, the human exposures at the RHD. A statistically significant incidence of thyroid parafollicular cell adenoma and carcinoma seen only in female rats at the high dose was within the range observed in historical controls.

Lamivudine: Long-term carcinogenicity studies with lamivudine in mice and rats showed no evidence of carcinogenic potential at exposures up to 10 times (mice) and 58 times (rats) the human exposures at the RHD.

TDF: Long-term oral carcinogenicity studies of TDF in mice and rats were carried out at exposures up to approximately 16 times (mice) and 5 times (rats) those observed in humans at the RHD. At the high dose in female mice, liver adenomas were increased at exposures 16 times of that in humans. In rats, the study was negative for carcinogenic findings at exposures up to 5 times that observed in humans at the RHD.

Mutagenesis

Doravirine: Doravirine was not genotoxic in a battery of in vitro or in vivo assays, including microbial mutagenesis, chromosomal aberration in Chinese hamster ovary cells, and in in vivo rat micronucleus assays.

Lamivudine: Lamivudine was mutagenic in an L5178Y mouse lymphoma assay and clastogenic in a cytogenetic assay using cultured human lymphocytes. Lamivudine was not mutagenic in a microbial mutagenicity assay, in an in vitro cell transformation assay, in a rat micronucleus test, in a rat bone marrow cytogenetic assay, and in an assay for unscheduled DNA synthesis in rat liver. Lamivudine showed no evidence of in vivo genotoxic activity in the rat at oral doses of up to 2,000 mg per kg, producing plasma levels of 35 to 45 times those in humans at the recommended dose for HIV-1 infection.

TDF: TDF was mutagenic in the in vitro mouse lymphoma assay and negative in an in vitro bacterial mutagenicity test (Ames test). In an in vivo mouse micronucleus assay, TDF was negative when administered to male mice.

Impairment of Fertility

Doravirine: There were no effects on fertility, mating performance or early embryonic development when doravirine was administered to rats up to the highest dose tested. Systemic exposures (AUC) to doravirine were approximately 7 times the exposure in humans at the RHD.

Lamivudine: In a study of reproductive performance, lamivudine administered to rats at doses up to 4,000 mg per kg per day, producing plasma levels 47 to 70 times those in humans, revealed no evidence of impaired fertility and no effect on the survival, growth, and development to weaning of the offspring.

TDF: There were no effects on fertility, mating performance or early embryonic development when TDF was administered to male rats at a dose equivalent to 10 times the RHD based on body surface area comparisons for 28 days prior to mating and to female rats for 15 days prior to mating through day 7 of gestation. There was, however, an alteration of the estrous cycle in female rats.

14 CLINICAL STUDIES

14.1 Clinical Trial Results in Adults with No Antiretroviral Treatment History

The efficacy of DELSTRIGO is based on the analyses of 96-week data from a randomized, multicenter, double-blind, active controlled Phase 3 trial (DRIVE-AHEAD, NCT02403674) in participants living with HIV with no antiretroviral treatment history (n=728).

Participants were randomized and received at least 1 dose of either DELSTRIGO or EFV 600 mg/FTC 200 mg/TDF 300 mg once daily. At baseline, the median age of participants was 31 years, 15% were female, 52% were Non-White, 3% had hepatitis B or C coinfection, 14% had a history of AIDS, 21% had HIV-1 RNA greater than 100,000 copies/mL, and 88% had CD4+ T-cell count greater than 200 cells/mm^3; these characteristics were similar between treatment groups. Week 96 outcomes for DRIVE-AHEAD are provided in Table 10.

Mean CD4+ T-cell counts in the DELSTRIGO and EFV/FTC/TDF groups increased from baseline by 238 and 223 cells/mm^3, respectively.

Table 10: Virologic Outcome in DRIVE-AHEAD at Week 96 in HIV-1 Adult Participants with No Antiretroviral Treatment History
Outcome | DELSTRIGO Once Daily N=364 | EFV/FTC/TDF Once Daily N=364
HIV-1 RNA <50 copies/mL | 77% | 74%
Treatment Difference (95% CI) [The 95% CI for the treatment difference was calculated using stratum-adjusted Mantel-Haenszel method.] | 3.8% (-2.4%, 10.0%)
HIV-1 RNA ≥ 50 copies/mL [Includes participants who discontinued study drug or study before Week 96 for lack or loss of efficacy and participants with HIV-1 RNA equal to or above 50 copies/mL in the Week 96 window.] | 15% | 12%
No Virologic Data at Week 96 Window | 7% | 14%
Discontinued study due to AE or Death [Includes participants who discontinued because of adverse event (AE) or death if this resulted in no virologic data in the Week 96 window.] | 3% | 8%
Discontinued study for Other Reasons [Other reasons include: lost to follow-up, non-compliance with study drug, physician decision, pregnancy, protocol deviation, screen failure, withdrawal by participant.] | 4% | 5%
On study but missing data in window | 1% | 1%
Proportion (%) of Participants With HIV-1 RNA <50 copies/mL at Week 96 by Baseline and Demographic Category
Gender
Male | 78% (N = 305) | 73% (N = 311)
Female | 75% (N = 59) | 75% (N = 53)
Race
White | 80% (N = 176) | 74% (N = 170)
Non-White | 76% (N = 188) | 74% (N = 194)
Ethnicity [Does not include participants whose ethnicity or viral subtypes were unknown.]
Hispanic or Latino | 81% (N = 126) | 77% (N = 119)
Not Hispanic or Latino | 76% (N = 238) | 72% (N = 239)
Baseline HIV-1 RNA (copies/mL)
≤100,000 copies/mL | 80% (N = 291) | 77% (N = 282)
>100,000 copies/mL | 67% (N = 73) | 62% (N = 82)
CD4+ T-cell Count (cells/mm^3)
≤200 cells/mm^3 | 59% (N = 44) | 70% (N = 46)
>200 cells/mm^3 | 80% (N = 320) | 74% (N = 318)
Viral Subtype
Subtype B | 80% (N = 232) | 72% (N = 253)
Subtype Non-B | 73% (N = 130) | 77% (N = 111)

14.2 Clinical Trial Results in Virologically-Suppressed Adults

The efficacy of switching from a baseline regimen consisting of two NRTIs in combination with a PI plus either ritonavir or cobicistat, or elvitegravir plus cobicistat, or an NNRTI to DELSTRIGO was evaluated in a randomized, open-label trial (DRIVE-SHIFT, NCT02397096), in virologically-suppressed adults living with HIV. Participants must have been virologically-suppressed (HIV-1 RNA <50 copies/mL) on their baseline regimen for at least 6 months prior to trial entry, with no history of virologic failure. Participants were randomized to either switch to DELSTRIGO at baseline [n = 447, Immediate Switch Group (ISG)], or stay on their baseline regimen until Week 24, at which point they switched to DELSTRIGO [n = 223, Delayed Switch Group (DSG)].

At baseline, the median age of participants was 43 years, 16% were female, and 24% were Non-White, 21% were of Hispanic or Latino ethnicity, 3% had hepatitis B and/or C virus co-infection, 17% had a history of AIDS, 96% had CD4+ T-cell count greater than or equal to 200 cells/mm^3, 70% were on a regimen containing a PI plus ritonavir, 24% were on a regimen containing an NNRTI, 6% were on a regimen containing elvitegravir plus cobicistat, and 1% were on a regimen containing a PI plus cobicistat; these characteristics were similar between treatment groups.

Virologic outcome results are shown in Table 11.

Table 11: Virologic Outcomes in DRIVE-SHIFT in HIV-1 Virologically-Suppressed Participants Who Switched to DELSTRIGO
Outcome | DELSTRIGO Once Daily ISG Week 48 N=447 | Baseline Regimen DSG Week 24 N=223
HIV-1 RNA ≥ 50 copies/mL [Includes participants who discontinued study drug or study before Week 48 for ISG or before Week 24 for DSG for lack or loss of efficacy and participants with HIV-1 RNA ≥50 copies/mL in the Week 48 window for ISG and in the Week 24 window for DSG] | 2% | 1%
ISG-DSG, Difference (95% CI) [The 95% CI for the treatment difference was calculated using stratum-adjusted Mantel-Haenszel method.] , [Assessed using a non-inferiority margin of 4%.] | 0.7% (-1.3%, 2.6%)
HIV-1 RNA <50 copies/mL | 91% | 95%
No Virologic Data Within the Time Window | 8% | 4%
Discontinued study due to AE or Death [Includes participants who discontinued because of adverse event (AE) or death if this resulted in no virologic data on treatment during the specified window.] | 3% | <1%
Discontinued study for Other Reasons [Other reasons include: lost to follow-up, non-compliance with study drug, physician decision, protocol deviation, withdrawal by participant.] | 4% | 4%
On study but missing data in window | 0 | 0
Proportion (%) of Participants With HIV-1 RNA <50 copies/mL by Baseline and Demographic Category
Age (years)
<50 | 90% (N = 320) | 95% (N = 157)
≥50 | 94% (N = 127) | 94% (N = 66)
Gender
Male | 91% (N = 372) | 94% (N = 194)
Female | 91% (N = 75) | 100% (N = 29)
Race
White | 90% (N = 344) | 95% (N = 168)
Non-White | 93% (N = 103) | 93% (N = 55)
Ethnicity
Hispanic or Latino | 88% (N = 99) | 91% (N = 45)
Not Hispanic or Latino | 91% (N = 341) | 95% (N = 175)
CD4+ T-cell Count (cells/mm^3)
<200 cells/mm^3 | 85% (N = 13) | 75% (N = 4)
≥200 cells/mm^3 | 91% (N = 426) | 95% (N = 216)
Baseline Regimen [Baseline Regimen = PI plus either ritonavir or cobicistat (specifically atazanavir, darunavir, or lopinavir), or elvitegravir plus cobicistat, or NNRTI (specifically efavirenz, nevirapine, or rilpivirine), each administered with two NRTIs.]
PI plus either ritonavir or cobicistat | 90% (N = 316) | 94% (N = 156)
elvitegravir plus cobicistat or NNRTI | 93% (N = 131) | 96% (N = 67)

14.3 Clinical Trial Results in Pediatric Participants

The efficacy of DELSTRIGO was evaluated in cohort 2 of an open-label, single-arm 2-cohort trial in pediatric participants 12 to less than 18 years of age living with HIV (IMPAACT 2014 (Protocol 027), NCT03332095). In cohort 1, virologically-suppressed participants (n=9) received a single 100 mg dose of doravirine followed by intensive PK sampling. In cohort 2, virologically-suppressed participants (n=43) were switched to DELSTRIGO and treatment-naïve participants (n=2) were started on DELSTRIGO.

In cohort 2, at baseline the median age of participants was 15 years (range: 12 to 17), the median weight was 52 kg (range: 45 to 80), 58% were female, 78% were Asian and 22% were Black, and the median CD4+ T-cell count was 713 cells per mm^3 (range 84 to 1397). After switching to DELSTRIGO, 95% (41/43) of virologically-suppressed participants remained suppressed (HIV-1 RNA <50 copies/mL) at Week 24. One of the two treatment-naïve participants achieved HIV-1 RNA <50 copies/mL at Week 24. The other treatment-naïve participant met the protocol-defined virologic failure criteria (defined as 2 consecutive plasma HIV-1 RNA test results ≥200 copies/mL at or after Week 24) and was evaluated for the development of resistance; no emergence of genotypic or phenotypic resistance to doravirine, lamivudine, or tenofovir was detected.

16 HOW SUPPLIED/STORAGE AND HANDLING

Each DELSTRIGO tablet contains 100 mg of doravirine, 300 mg of lamivudine, and 300 mg of tenofovir disoproxil fumarate (equivalent to 245 mg of tenofovir disoproxil), is yellow, oval-shaped, film-coated, and is debossed with the corporate logo and 776 on one side and plain on the other side. Each bottle contains 30 tablets (NDC 0006-5007-01) and silica gel desiccants, and is closed with a child-resistant closure.

STORAGE AND HANDLING

Store DELSTRIGO in the original bottle. Keep the bottle tightly closed to protect from moisture. Do not remove the desiccants.

Store DELSTRIGO at 20°C to 25°C (68°F to 77°F); excursions permitted to 15°C to 30°C (59°F to 86°F) [see USP Controlled Room Temperature].

17 PATIENT COUNSELING INFORMATION

Advise the patient to read the FDA-approved patient labeling (Patient Information).

Severe Skin Reactions

Inform patients that severe skin reactions including Stevens-Johnson syndrome (SJS)/toxic epidermal necrolysis (TEN) have been reported with DELSTRIGO. Advise patients to immediately contact their healthcare provider if they develop a rash. Instruct patients to immediately stop taking DELSTRIGO and seek medical attention if a painful rash with mucosal involvement develops [see Warnings and Precautions (5.1)].

Severe Acute Exacerbation of Hepatitis B in people with concomitant HIV-1 and HBV

Inform patients that severe acute exacerbations of hepatitis B have been reported in people with concomitant HIV-1 and HBV who have discontinued lamivudine or TDF and may occur with discontinuation of DELSTRIGO [see Warnings and Precautions (5.2)]. Advise patients not to discontinue DELSTRIGO without first informing their healthcare provider.

Drug Interactions

Inform patients that DELSTRIGO may interact with certain other drugs; therefore, advise patients to report to their healthcare provider the use of any other prescription or nonprescription medication or herbal products, including St. John's wort [see Contraindications (4), Warnings and Precautions (5.4), and Drug Interactions (7)].

For patients concomitantly receiving rifabutin, take one tablet of doravirine (PIFELTRO) 100 mg approximately 12 hours after the dose of DELSTRIGO [see Dosage and Administration (2.4)].

New Onset or Worsening Renal Impairment

Inform patients that renal impairment, including cases of acute renal failure and Fanconi syndrome, has been reported in association with the use of TDF. Advise patients to avoid DELSTRIGO with concurrent or recent use of a nephrotoxic agent (e.g., high-dose or multiple NSAIDS) [see Warnings and Precautions (5.3)].

Bone Loss and Mineralization Defects

Inform patients that decreases in bone mineral density have been observed with the use of TDF, a component of DELSTRIGO. Assessment of bone mineral density (BMD) should be considered in patients who have a history of pathologic bone fracture or other risk factors for osteoporosis or bone loss [see Warnings and Precautions (5.5)].

Immune Reconstitution Syndrome

Inform patients that in some patients with advanced HIV infection (AIDS), signs and symptoms of inflammation from previous infections may occur soon after anti-HIV treatment is started. It is believed that these symptoms are due to an improvement in the body's immune response, enabling the body to fight infections that may have been present with no obvious symptoms. Advise patients to inform their healthcare provider immediately of any symptoms of infection [see Warnings and Precautions (5.6)].

Dosing Instructions

Advise patients to take DELSTRIGO every day at a regularly scheduled time with or without food. Inform patients that it is important not to miss or skip doses as it can result in development of resistance. If a patient forgets to take DELSTRIGO, tell the patient to take the missed dose right away, unless it is almost time for the next dose. Advise the patient not to take 2 doses at one time and to take the next dose at the regularly scheduled time.

Pregnancy Registry

Inform patients that there is an antiretroviral pregnancy registry to monitor fetal outcomes of pregnant individuals exposed to DELSTRIGO [see Use in Specific Populations (8.1)].

Lactation

Inform individuals with HIV-1 infection that the potential risks of breastfeeding include: (1) HIV-1 transmission (in HIV-1-negative infants), (2) developing viral resistance (in HIV-1-positive infants), and (3) serious adverse reactions in a breastfed infant similar to those seen in adults [see Use in Specific Populations (8.2)].

Manufactured for: Merck Sharp & Dohme LLC
Rahway, NJ 07065, USA

For patent information: www.msd.com/research/patent

The trademarks depicted herein are owned by their respective companies.

Copyright © 2018-2025 Merck & Co., Inc., Rahway, NJ, USA, and its affiliates.
All rights reserved.

uspi-mk1439a-t-2510r010

Patient Information
DELSTRIGO® (del-STREE-go)
(doravirine, lamivudine, and tenofovir disoproxil fumarate)
tablets

What is the most important information I should know about DELSTRIGO?

DELSTRIGO can cause serious side effects, including:
Worsening of hepatitis B virus infection (HBV). If you have Human Immunodeficiency Virus-1 (HIV-1) and HBV infection, your HBV infection may get worse (flare-up) if you stop taking DELSTRIGO. A "flare-up" is when your HBV infection suddenly returns in a worse way than before. Your healthcare provider will test you for HBV infection before you start treatment with DELSTRIGO.

- Do not run out of DELSTRIGO. Refill your prescription or talk to your healthcare provider before your DELSTRIGO is all gone.
- Do not stop taking DELSTRIGO without first talking to your healthcare provider. If you stop taking DELSTRIGO, your healthcare provider will need to check your health often and do blood tests regularly for several months to check your liver. Tell your healthcare provider about any new or unusual symptoms you may have after you stop taking DELSTRIGO.

For more information about side effects, see "What are the possible side effects of DELSTRIGO?"

What is DELSTRIGO?

DELSTRIGO is a prescription medicine that is used without other HIV-1 medicines to treat HIV-1 infection in adults and children who weigh at least 77 pounds (35 kg):

- who have not received HIV-1 medicines in the past, or
- to replace their current HIV-1 medicines for people whose healthcare provider determines that they meet certain requirements.

HIV-1 is the virus that causes Acquired Immune Deficiency Syndrome (AIDS).

DELSTRIGO contains the prescription medicines doravirine, lamivudine and tenofovir disoproxil fumarate.

It is not known if DELSTRIGO is safe and effective in children who weigh less than 77 pounds (35 kg).

Who should not take DELSTRIGO?

Do not take DELSTRIGO if you take any of the following medicines:

- carbamazepine
- oxcarbazepine
- phenobarbital
- phenytoin
- enzalutamide

- rifampin
- rifapentine
- mitotane
- St. John's wort

Ask your healthcare provider or pharmacist if you are not sure if your medicine is one that is listed above. If you have taken any of the medicines in the past 4 weeks, talk to your healthcare provider or pharmacist before starting treatment with DELSTRIGO.

Do not take DELSTRIGO if you have ever had an allergic reaction to lamivudine.

What should I tell my healthcare provider before treatment with DELSTRIGO?

Before treatment with DELSTRIGO, tell your healthcare provider about all of your medical conditions, including if you:

- have hepatitis B virus infection
- have kidney problems
- have bone problems, including a history of bone fractures
- are pregnant or plan to become pregnant. It is not known if DELSTRIGO can harm your unborn baby. Tell your healthcare provider if you become pregnant during treatment with DELSTRIGO.
  Pregnancy Registry: There is a pregnancy registry for people who take DELSTRIGO during pregnancy. The purpose of this registry is to collect information about the health of you and your baby. Talk to your healthcare provider about how you can take part in this registry.
- are breastfeeding or plan to breastfeed. Two of the medicines in DELSTRIGO (lamivudine and tenofovir) can pass into your breast milk. Doravirine may pass to your baby in your breast milk. Talk with your healthcare provider about the following risks to your baby from breastfeeding during treatment with DELSTRIGO:
  - the HIV-1 virus may pass to your baby if your baby does not have HIV-1 infection.
  - the HIV-1 virus may become harder to treat if your baby has HIV-1 infection.
  - your baby may get side effects from DELSTRIGO.

Tell your healthcare provider about all the medicines you take, including prescription and over-the-counter medicines, vitamins, and herbal supplements.

- Some medicines interact with DELSTRIGO. Keep a list of your medicines to show your healthcare provider and pharmacist.
- Tell your healthcare provider if you have taken rifabutin in the past 4 weeks.
- You can ask your healthcare provider or pharmacist for a list of medicines that interact with DELSTRIGO.
- Do not start taking a new medicine without telling your healthcare provider. Your healthcare provider can tell you if it is safe to take DELSTRIGO with other medicines.

How should I take DELSTRIGO?

- Take DELSTRIGO every day exactly as your healthcare provider tells you to take it.
- Take DELSTRIGO 1 time each day, at about the same time every day.
- DELSTRIGO is usually taken by itself (without other HIV-1 medicines).
- If you take the medicine rifabutin during treatment with DELSTRIGO, your healthcare provider will also prescribe an additional dose of doravirine for you. You may not have enough doravirine in your blood if you take rifabutin during treatment with DELSTRIGO. Carefully follow your healthcare provider's instructions about when to take doravirine and how much to take. This is usually 1 tablet of doravirine about 12 hours after your last dose of DELSTRIGO.
- Take DELSTRIGO with or without food.
- Do not change your dose or stop taking DELSTRIGO without talking to your healthcare provider. Stay under a healthcare provider's care when taking DELSTRIGO.
- It is important that you do not miss or skip doses of DELSTRIGO.
- If you miss a dose of DELSTRIGO, take it as soon as you remember. If it is almost time for your next dose, skip the missed dose and take the next dose at your regular time. Do not take 2 doses of DELSTRIGO at the same time.
- If you have any questions, call your healthcare provider or pharmacist.
- If you take too much DELSTRIGO, call your healthcare provider or go to the nearest hospital emergency room right away.
- When your DELSTRIGO supply starts to run low, get more from your healthcare provider or pharmacy. This is very important because the amount of virus in your blood may increase if the medicine is stopped for even a short time. The virus may develop resistance to DELSTRIGO and become harder to treat.

What are the possible side effects of DELSTRIGO?

DELSTRIGO may cause serious side effects, including:

- See "What is the most important information I should know about DELSTRIGO?"
- Severe skin reactions have happened in people treated with DELSTRIGO. Call your healthcare provider right away if you develop a rash during treatment with DELSTRIGO. Stop taking DELSTRIGO and get medical help right away if you develop a painful rash with any of the following symptoms: fever, blisters or sores in the mouth, blisters or peeling of the skin, or redness or swelling of the eyes (conjunctivitis).
- New or worse kidney problems, including kidney failure. Your healthcare provider should do blood and urine tests to check your kidneys before you start and during treatment with DELSTRIGO. Your healthcare provider may tell you to stop taking DELSTRIGO if you develop new or worse kidney problems.
- Bone problems can happen in some people who take DELSTRIGO. Bone problems include bone pain, softening or thinning (which may lead to fractures). Your healthcare provider may need to do tests to check your bones.

Tell your healthcare provider if you have any of the following symptoms during treatment with DELSTRIGO: bone pain that does not go away or worsening bone pain, pain in your arms, legs, hands or feet, broken (fractured) bones, or muscle pain or weakness. These may be symptoms of a bone or kidney problem.

- Changes in your immune system (Immune Reconstitution Syndrome) can happen when you start taking HIV-1 medicines. Your immune system may get stronger and begin to fight infections that have been hidden in your body for a long time. Tell your healthcare provider right away if you start having any new symptoms after starting your HIV-1 medicine.

The most common side effects of DELSTRIGO include dizziness, nausea, and abnormal dreams.

These are not all of the possible side effects of DELSTRIGO.
Call your doctor for medical advice about side effects. You may report side effects to FDA at 1-800-FDA-1088.

How should I store DELSTRIGO?

- Store DELSTRIGO tablets at room temperature between 68°F to 77°F (20°C to 25°C).
- Keep DELSTRIGO in the original bottle.
- Do not take the tablets out of the bottle to store in another container, such as a pill box.
- Keep the bottle tightly closed to protect DELSTRIGO from moisture.
- The DELSTRIGO bottle contains desiccants to help keep your medicine dry (protect it from moisture). Keep the desiccants in the bottle. Do not eat the desiccants.

Keep DELSTRIGO and all medicines out of the reach of children.

General information about the safe and effective use of DELSTRIGO.

Medicines are sometimes prescribed for purposes other than those listed in the Patient Information leaflet. Do not use DELSTRIGO for a condition for which it was not prescribed. Do not give DELSTRIGO to other people, even if they have the same symptoms that you have. It may harm them. You can ask your pharmacist or healthcare provider for information about DELSTRIGO that is written for healthcare professionals.

What are the ingredients in DELSTRIGO?

Active ingredients: doravirine, lamivudine, and tenofovir disoproxil fumarate.

Inactive ingredients: colloidal silicon dioxide, croscarmellose sodium, hypromellose acetate succinate, magnesium stearate, microcrystalline cellulose, and sodium stearyl fumarate. The tablet film coating contains hypromellose, iron oxide yellow, lactose monohydrate, titanium dioxide, and triacetin. The coated tablets are polished with carnauba wax.

Manufactured for: Merck Sharp & Dohme LLC
Rahway, NJ 07065, USA

For patent information: www.msd.com/research/patent
The trademarks depicted herein are owned by their respective companies.
Copyright © 2018-2024 Merck & Co., Inc., Rahway, NJ, USA, and its affiliates.
All rights reserved.
usppi-mk1439a-t-2411r005

For more information, go to www.DELSTRIGO.com or call 1-877-888-4231.

This Patient Information has been approved by the U.S. Food and Drug Administration.

Revised: 11/2024

PRINCIPAL DISPLAY PANEL - 30 Tablet Bottle Label

NDC 0006-5007-01

Delstrigo®
(doravirine, lamivudine, and
tenofovir disoproxil fumarate) tablets

100mg/300mg /300mg

Each tablet contains 100 mg doravirine, 300 mg
lamivudine, and 300 mg tenofovir disoproxil fumarate
(equivalent to 245 mg tenofovir disoproxil).

ALERT: Find out about medicines that
should NOT be taken with Delstrigo®.

Rx only

30 Tablets